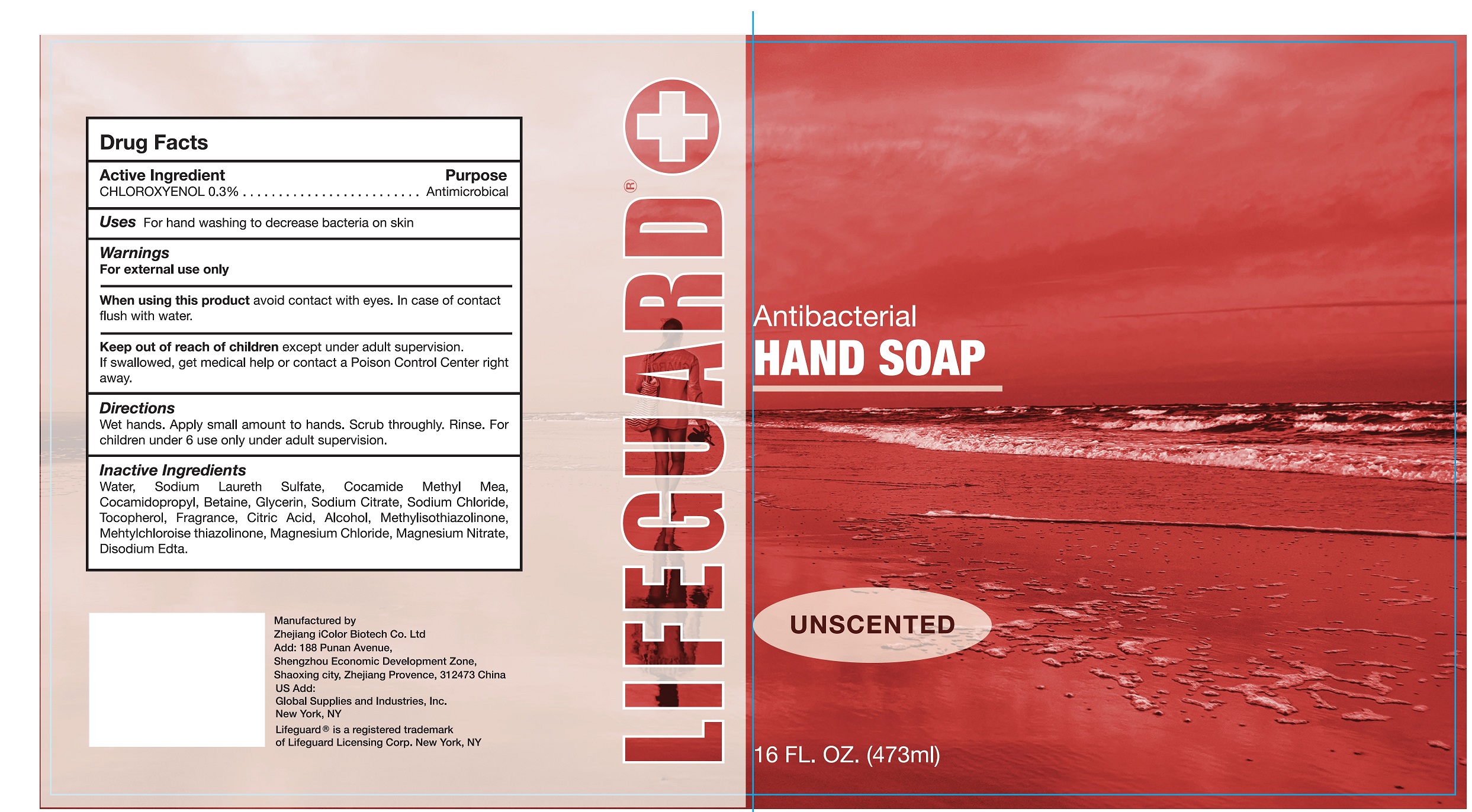 DRUG LABEL: LFG
NDC: 77879-006 | Form: LIQUID
Manufacturer: BT Supplies West Inc
Category: otc | Type: HUMAN OTC DRUG LABEL
Date: 20220209

ACTIVE INGREDIENTS: CHLOROXYLENOL 3 mg/1 mL
INACTIVE INGREDIENTS: WATER; SODIUM LAURETH SULFATE; COCOYL METHYL MONOETHANOLAMINE; COCAMIDOPROPYL BETAINE; GLYCERIN; SODIUM CITRATE; SODIUM CHLORIDE; TOCOPHEROL; CITRIC ACID MONOHYDRATE; ALCOHOL; METHYLISOTHIAZOLINONE; METHYLCHLOROISOTHIAZOLINONE; MAGNESIUM CHLORIDE; MAGNESIUM NITRATE; EDETATE DISODIUM ANHYDROUS

LFG-SOAP Soap

Active Ingredient

CHLOROXYLENOL 0.3%

Purpose

Antimicrobical

Uses

For hand washing to decrease bacteria on skin

Warnings

For external use only

When using this product

avoid contact with eyes. In case of contact flush with water.

Keep out of reach of children.

except under adult supervision. If swallowed, get medical help or contact a Poison Control Center right away.

Directions

Wet hands. Apply small amount to hands. Scrub thoroughly. Rinse. For children under 6 use only under adult supervision.

Inactive Ingredients

Water, Sodium Laureth Sulfate, Cocamide Methyl Mea, Cocamidopropyl Betaine, Glycerin, Sodium Citrate, Sodium Chloride, Tocopherol, Fragrance, Citric Acid, Alcohol, Methylisothiazolinone, Methylchloroise thiazolinone, Magnesium Chloride, Magnesium Nitrate, Disodium Edita.